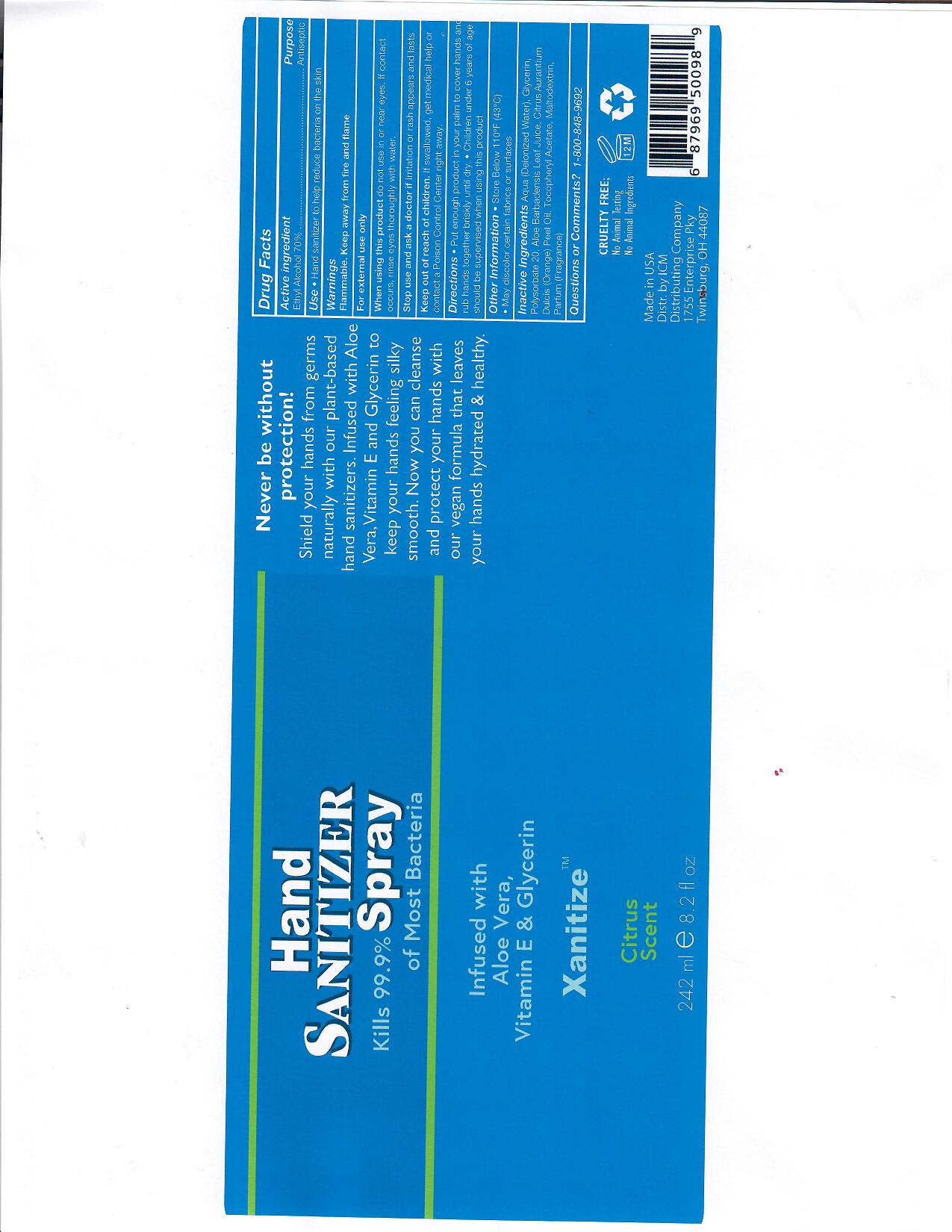 DRUG LABEL: Xanitize
NDC: 77516-111 | Form: SOLUTION
Manufacturer: ICM Distributing Company, INC
Category: otc | Type: HUMAN OTC DRUG LABEL
Date: 20200513

ACTIVE INGREDIENTS: ALCOHOL 70 mL/100 mL
INACTIVE INGREDIENTS: GLYCERIN; ALOE; WATER; POLYSORBATE 20; ORANGE PEEL; MALTODEXTRIN

This is a hand sanitizer manufactured according to the Temporary Policy for Preparation of Certain Alcohol-Based Hand Sanitizer Products During the Public Health Emergency (CoViD-19); Guidance for Industry.

Active Ingredient(s)

Ethyl Alcohol 70% v/v. Purpose: Antiseptic

Purpose

Antiseptic, Hand Sanitizer

Use

Hand Sanitizer to help reduce bacteria on the skin.

Warnings

For external use only. Flammable. Keep away from fire or flame

Do not use

- in children less than 2 months of age
- on open skin wounds

When using this product do not use in or near eyes. If contact occurs, rinse eyes thoroughly with water.
Stop use and ask a doctor if irritation or rash occurs. These may be signs of a serious condition.
Keep out of reach of children. If swallowed, get medical help or contact a Poison Control Center right away.

Stop use and ask a doctor if irritation or rash occurs.

Keep out of reach of children. If swallowed, get medical help or contact a Poison Control Center right away.

Directions

- Place enough product in your palm to cover hands and rub hands together briskly until dry.
- Supervise children under 6 years of age when using this product to avoid swallowing.

Other information

- Store below 110°F (43°C)

Inactive ingredients

deionized water, glycerin, polysorbate 20, aloe leaf juice, orange peel oil, tocopheryl acetate, maltodextrin, parfum